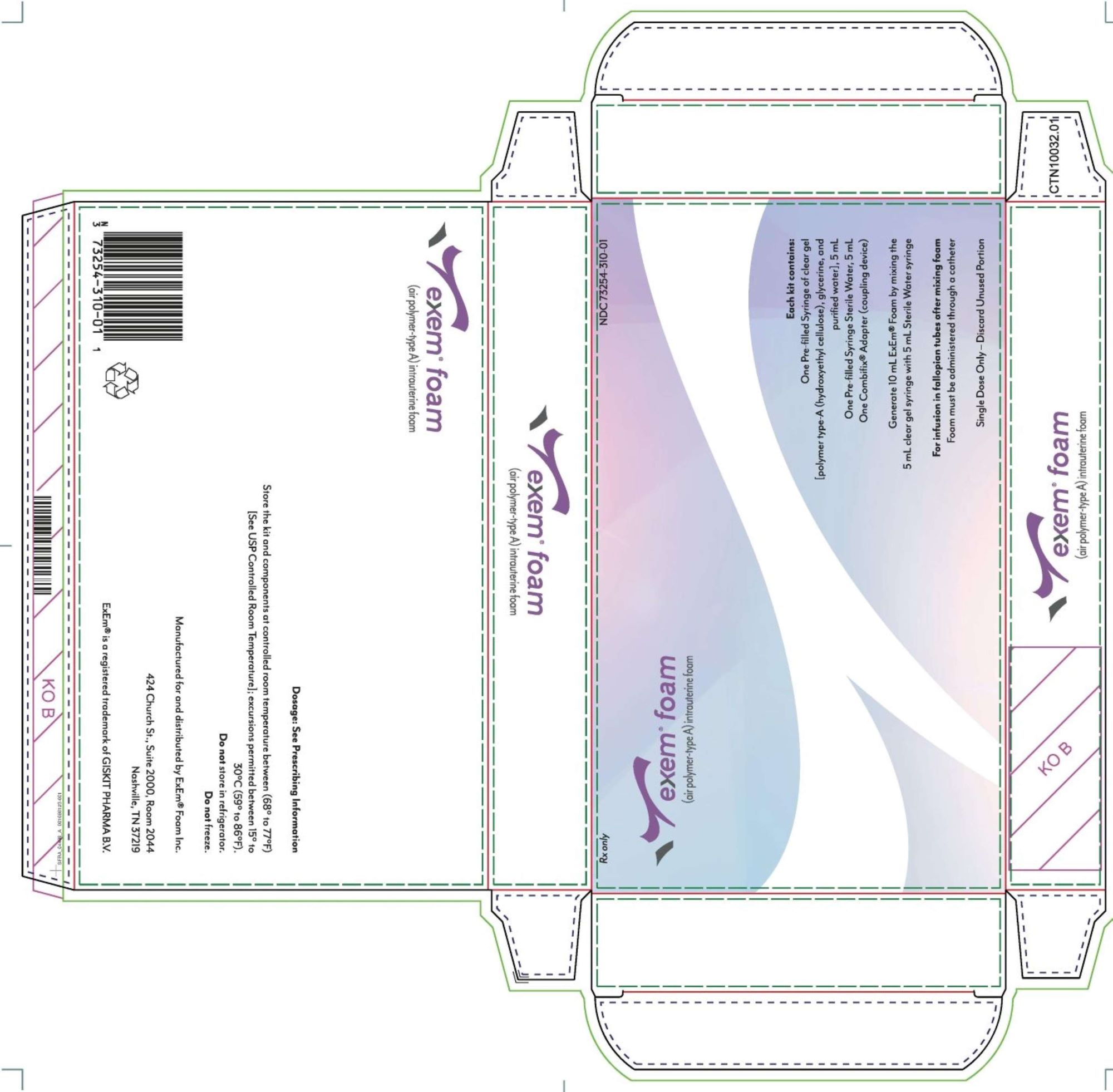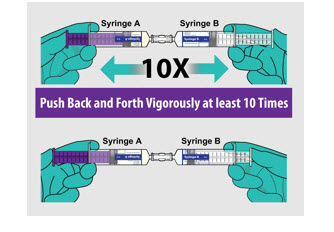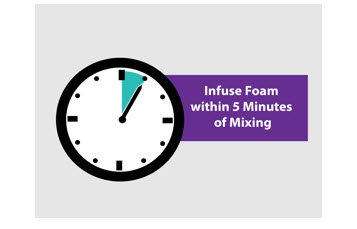 DRUG LABEL: ExEm Foam
NDC: 73254-310 | Form: KIT | Route: INTRAUTERINE
Manufacturer: GISKIT PHARMA B.V.
Category: prescription | Type: HUMAN PRESCRIPTION DRUG LABEL
Date: 20231108

ACTIVE INGREDIENTS: GLYCERIN 434.8 mg/5 mL; HYDROXYETHYL CELLULOSE (5500 MPA.S AT 2%) 80.97 mg/5 mL; WATER 5 mL/5 mL
INACTIVE INGREDIENTS: WATER

HIGHLIGHTS OF PRESCRIBING INFORMATION

These highlights do not include all the information needed to use EXEM® FOAM safely and effectively. See full prescribing information for EXEM® FOAM.
EXEM FOAM (air polymer-type A) intrauterine foam
Initial U.S. Approval: 2019

1 INDICATIONS AND USAGE

ExEm® Foam is an ultrasound contrast agent indicated for sonohysterosalpingography to assess fallopian tube patency in women with known or suspected infertility. (1)

2 DOSAGE AND ADMINISTRATION

- Confirm the patient is not pregnant prior to ExEm Foam administrations (2.1)
- Recommended dose is 2 mL to 3 mL of ExEm Foam by intrauterine infusion using a 5-Fr or larger catheter. Dose may be repeated in 2 mL to 3 mL increments, as needed, to achieve visualization of the fallopian tubes. Maximum total dose is 10 mL (2.2)
- See Full Prescribing Information for preparation and administration instructions. (2.3)

3 DOSAGE FORMS AND STRENGTHS

Intrauterine Foam, single-dose kit containing:

- one syringe with 5 mL clear Gel [polymer type A (hydroxyethyl cellulose), glycerin and purified water]
- one syringe with 5 mL Sterile Purified Water
- one Combifix® Adaptor (coupling device) (3)

4 CONTRAINDICATIONS

- ExEm Foam is contraindicated in:
  - Pregnancy (4)
  - Patients with known or suspected lower genital tract inflammation or infection (4)
  - Patients who have had a gynecologic procedure within the last 30 days (4)
  - Patients with vaginal bleeding (4)
  - Patient with known or suspected reproductive tract neoplasia. (4)

5 WARNINGS AND PRECAUTIONS

- Risk for fetal harm: Confirm that the patient has a negative pregnancy test within the 24 hours before ExEm Foam administration and confirm that the patient is in the pre-ovulatory phase of her menstrual cycle (cycle days 6 through 11). (4, 5.1)
- Risk for Post-Procedure Gynecologic Infections: Do not use in contraindicated situations even if the patient is receiving antimicrobial therapy. (4, 5.2)

6 ADVERSE REACTIONS

Common adverse reactions are: pelvic and abdominal pain; vasovagal reactions and associated symptoms such as nausea and faintness; and post-procedure spotting. (6.1)

To report SUSPECTED ADVERSE REACTIONS, contact ExEm Foam Inc. at 1-844-963-EXEM (1-844-963-3936) or FDA at 1-800-FDA-1088 or www.fda.gov/medwatch.

FULL PRESCRIBING INFORMATION

1 INDICATIONS AND USAGE

ExEm® Foam is indicated for sonohysterosalpingography to assess fallopian tube patency in women with known or suspected infertility.

2 DOSAGE AND ADMINISTRATION

2.1 Important Pre-Administration Information

To ensure that the patient is not pregnant prior to ExEm Foam administration [see Contraindications (4) and Warnings and Precautions (5.1)]:

- Confirm that the patient has a negative pregnancy test within the 24 hours before ExEm Foam administration .
- Confirm the patient is in the pre-ovulatory phase of her menstrual cycle (cycle days 6 through 11).

2.2 Recommended Dosage

- The recommended initial dose of ExEm Foam is 2 mL to 3 mL by intrauterine infusion using a 5-Fr or larger catheter with luer connection.
- The dose may be repeated in increments of 2 mL to 3 mL, as needed, to achieve visualization of the fallopian tubes.
- Maximum total dose is 10 mL.

2.3 Preparation and Administration

The ExEm Foam kit includes the following components:

- Syringe A containing 5 mL clear Gel [polymer type A (hydroxyethyl cellulose), glycerin and purified water]
- Syringe B containing 5 mL Sterile Purified Water
- Combifix Adapter (coupling device)

Preparation

- Examine the package and do not use if package has been previously opened or damaged.
- Ensure the kit is at room temperature.
- Handle products following aseptic practices (e.g. sterile gloves).
- Generate foam by mixing Syringe A (Gel) with Syringe B (Sterile Purified Water) included in the package as described in Figure 1.
- Infuse foam within 5 minutes of reconstitution.

FIGURE 1: Reconstitution of ExEm Foam

- Unscrew and discard the caps from each syringe when ready to prepare the foam.
- Push and screw Syringe A to one end of the Combifix Adapter.
- Push and screw Syringe B to the other end of the Combifix Adapter.
- Make sure these syringes are attached tightly to avoid loss of liquid when mixing.
- Push the plunger of one syringe vigorously to transfer, and begin mixing the contents from one syringe to the other syringe. Repeat this process at least 10 times.
- The reconstituted foam is completely milky white (opaque) in color
- After mixing, transfer all of the foam into one syringe, then disconnect the adapter and other syringe.
- Approximately 10 mL of ExEm Foam is created by mixing Syringe A of clear Gel with Syringe B of Sterile Purified Water.
- Infuse within 5 minutes of mixing to ensure adequate imaging.

Administration

- Administer through a 5-Fr or larger catheter with luer connection only. If there is resistance when infusing foam use a larger catheter. Do not infuse forcefully.
- Infuse 1 mL of foam to confirm proper placement of the catheter tip in the cervix and access to the uterine cavity.
- Slowly infuse 2 mL to 3 mL of the foam at a time to avoid patient discomfort.
- Discard unused portion after use.

2.4 Imaging Guidance

Conduct transvaginal ultrasound imaging in accordance with ultrasound manufacturer recommendations.

ExEm Foam in the fallopian tube will appear as an echogenic line along the length of the tube on the image.

A fallopian tube is classified as patent if ExEm Foam is observed to pass from the tube and spill into the peritoneal cavity. The tube will appear as a thin, bright line.

A fallopian tube is classified as occluded if ExEm Foam is not observed to pass from the tube and spill into the peritoneal cavity. As secondary findings, (1) there may be no bright line due to no flow into the fallopian tube, or (2) the tubal lumen may appear distended and contrast ﬂow might be observed only in the intramural or isthmic part of the tube.

3 DOSAGE FORMS AND STRENGTHS

Intrauterine Foam, single-dose kit containing:

- Syringe A: one syringe with 5 mL clear Gel [polymer-type A (hydoxyethyl cellulose), glycerin and purified water]
- Syringe B: one syringe with 5 mL Sterile Purified Water
- One Combifix Adaptor (coupling device)

When prepared as directed ExEm Foam will contain between 10,000 to 127,000 bubbles per mL.

4 CONTRAINDICATIONS

ExEm Foam is contraindicated for use in:

- Pregnancy [see Warnings and Precautions (5.1)] .
- Patients with known or suspected lower genital tract inflammation or infection [see Warnings and Precautions (5.2)].
- Patients who have had a gynecologic procedure within the last 30 days [see Warnings and Precautions (5.2)].
- Patients with vaginal bleeding
  - Due to the risk of intravasation of ExEm Foam as a result of exposure of the endometrial vessels during bleeding, and
  - Due to the potential risk of endometriosis as a result of seeding the peritoneum with endometrial tissue.
- Patients with known or suspected reproductive tract neoplasia due to the risk of peritoneal spread of neoplasm .

5 WARNINGS AND PRECAUTIONS

5.1 Risk for Fetal Harm

ExEm Foam is contraindicated for use in pregnancy due to the potential risk of fetal harm from an intrauterine procedure. To ensure that the patient is not pregnant prior to ExEm Foam administration, confirm that the patient has a negative pregnancy test within the 24 hours before ExEm Foam administration and confirm that the patient is in the pre-ovulatory phase of her menstrual cycle (cycle days 6 through 11) [see Contraindications (4)].

5.2 Risk for Post-Procedure Gynecologic Infections

There is a risk of post-procedure gynecological infections when ExEm Foam is used in sonohysterosalpingography. ExEm Foam is contraindicated for use in patients with known or suspected genital tract inflammation or infections (e.g. including pelvic inflammatory disease (PID) or suspected sexually transmitted disease) even if the patient is receiving antimicrobial therapy. ExEm Foam is contraindicated in patients who have had a gynecologic procedure within the past 30 days (e.g. curettage or conization) due to the risk of post-procedure infections [see Contraindications (4) and Adverse Reactions (6.2)] .

6 ADVERSE REACTIONS

6.1 Clinical Trials Experience

Because clinical trials are conducted under widely varying conditions, adverse reaction rates observed in the clinical trials of a drug may not reflect the rates observed in practice.

The common adverse reactions associated with ExEm Foam when used as indicated in sonohysterosalpingography are: pelvic and abdominal pain; vasovagal reactions and associated symptoms such as nausea and faintness; and post-procedure spotting.

6.2 Postmarketing Experience

The following adverse reactions have been identified during post-approval use of (air polymer-type A) intrauterine foam outside of the United States. Because these reactions are reported voluntarily from a population of uncertain size, it is not always possible to reliably estimate their frequency or establish a causal relationship to drug exposure.

Gynecologic Infections: pelvic inflammatory disease, salpingitis, and tubo-ovarian abscess

8 USE IN SPECIFIC POPULATIONS

8.1 Pregnancy

Risk Summary

ExEm Foam is contraindicated for use in pregnancy due to the potential risk to the fetus from an intrauterine procedure [see Contraindications (4) and Warnings and Precautions (5.1)] . There are no available data on the use of ExEm Foam in pregnant women. Animal reproduction studies have not been conducted with ExEm Foam.

8.2 Lactation

Risk Summary

There are no data on the presence of the components used to generate ExEm Foam (glycerin and hydroxyethyl cellulose) in human milk, the effects on the breastfed infant, or the effects on milk production. No adverse effects in breastfed infants are anticipated following maternal administration of ExEm Foam, based on the wide safety margin for glycerol in infants and the expected negligible absorption of hydroxyethyl cellulose [see Clinical Pharmacology (12.3)]. The developmental and health benefits of breastfeeding should be considered along with the mother's clinical need for ExEm Foam and any potential adverse effects on the breastfed infant from ExEm Foam or from the underlying maternal condition.

8.3 Females and Males of Reproductive Potential

Confirm that the patient has a negative pregnancy test within the 24 hours before ExEm Foam administration [see Dosage and Administration (2.1) and Use in Specific Populations (8.1)].

8.4 Pediatric Use

The safety and effectiveness of ExEm Foam have not been established in pediatric patients.

11 DESCRIPTION

ExEm Foam (air polymer-type A) intrauterine foam, is an ultrasound contrast agent. It is provided to the user for preparation as a single-dose kit containing:

- 5 mL sterile clear Gel [polymer-type A (80.97 mg hydroxyethyl cellulose), 434.80 mg glycerin 85%, and purified water]; with a pH of 6 to 7.5.
- 5 mL Sterile Purified Water; with a pH of 6 to 7.5.

After preparation, ExEm Foam is a milky-white, water-soluble intrauterine foam with an osmolality of approximately 462 mOsm and will contain between 10,000 to 127,000 bubbles per mL with a median size of 45.6 to 60.6 micrometers (for bubbles between 20 to 200 micrometers).

12 CLINICAL PHARMACOLOGY

12.1 Mechanism of Action

ExEm Foam (air polymer-type A) intrauterine foam is formed by mixing the clear Gel [polymer-type A (hydroxyethyl cellulose), glycerin, and purified water] with air and Sterile Purified Water, creating an echogenic contrast agent. When visualized with ultrasound, the foam appears echogenic or bright within the fallopian tubes and peritoneal cavity.

12.2 Pharmacodynamics

ExEm Foam has no known pharmacological activity.

12.3 Pharmacokinetics

Assuming that a full 10 mL of ExEm Foam is used, and all glycerol is absorbed, the normal fasting endogenous glycerol plasma levels would not be affected. No literature data is found on absorption of hydroxyethyl cellulose (HEC) from the female reproductive tract and peritoneum. HEC is poorly permeable across GI epithelial mucosa; therefore, HEC is expected to exhibit very low permeability after administration and to produce negligible HEC systemic exposure.

The metabolism and excretion of HEC are not known.

13 NONCLINICAL TOXICOLOGY

No nonclinical toxicology studies have been conducted with ExEm Foam. Glycerol-hydroxyethyl cellulose (HEC) Gel is not genotoxic (Ames test) or cytotoxic (mouse lymphoma L5178Y TK+/- assay).

14 CLINICAL STUDIES

Clinical studies reported in the scientific literature have assessed the performance of sonohysterosalpingography with ExEm Foam (a technique referred to as HyFoSy) for the diagnosis of tubal patency in women with infertility. The studies used laparoscopy with chromotubation as the reference standard.

Study A compared 2D- and 3D-HyFoSy to previous laparoscopy with chromotubation in 50 women (median age 35 years) with at least 12 months of infertility (median duration of infertility 28 months). The women were randomly assigned to either HyFoSy with 2D imaging or HyFoSy with 3D imaging. The operator performing HyFoSy was blinded to the laparoscopy results. For 2D imaging, the proportion of fallopian tubes correctly identified as occluded was 80% and the proportion of tubes that were correctly identified as patent was 92%. For 3D imaging, the proportion of tubes correctly identified as occluded was 98% and the proportion of tubes that were correctly identified as patent was 91%.

Study B compared the diagnostic performance of HyFoSy with ExEm Foam using both 2D/3D-sonohysterosalpingography (2D/3D-HyFoSy) and 2D/3D-HyFoSy with high-definition flow Doppler enhancement (2D/3D-HDF-HyFoSy), to the reference standard of laparoscopy with chromotubation to establish the patency of the tubes. The study evaluated 132 women (259 fallopian tubes) with history of primary or secondary infertility who were consecutively enrolled over a period of 2 years. The mean age was 32 years and the mean duration of infertility was 2.6 years. The performance of 2D/3D-HyFoSy was similar to that of 2D/3D-HDF-HyFoSy. The performance estimates in Study B were numerically similar to those reported in Study A.

16 HOW SUPPLIED/STORAGE AND HANDLING

Supplied

ExEm Foam is supplied as a single-dose kit, NDC 73254-310-01. Each kit contains:

- Syringe A: One sterile syringe containing 5 mL of clear Gel [polymer-type A (hydroxyethyl cellulose), glycerin and purified water
- Syringe B: One sterile syringe containing 5 mL of Sterile Purified Water
- One sterile Combifix Adaptor (coupling device)

Storage and Handling

Store the kit and components at controlled room temperature between 20° to 25°C (68° to 77°F); [see USP Controlled Room Temperature]; excursions permitted at 15° to 30°C (59° to 86°F). Do not store in refrigerator. Do not freeze.

17 PATIENT COUNSELING INFORMATION

Risk for Post-Procedure Gynecologic Infections

Patients should be counseled regarding the risk of post-procedure gynecologic infections. Instruct patients to report to their healthcare provider any continued pelvic and abdominal pain, significant vaginal discharge and/or fever post-procedure [see Warnings and Precautions (5.2) and Adverse Reactions (6.2)] .

Abdominal and Pelvic Pain

Inform patients of the potential for transient abdominal and pelvic pain during and after ExEm Foam sonohysterosalpingography [see Adverse Reactions (6.1)]

Manufactured for and Distrbuted By: ExEm Foam Inc.

424 Church St., Suite 2000, Room 2044

Nashville, TN 37219

ExEm® is a registered trademark of GISKIT PHARMA B.V.

Revised: 4/2022